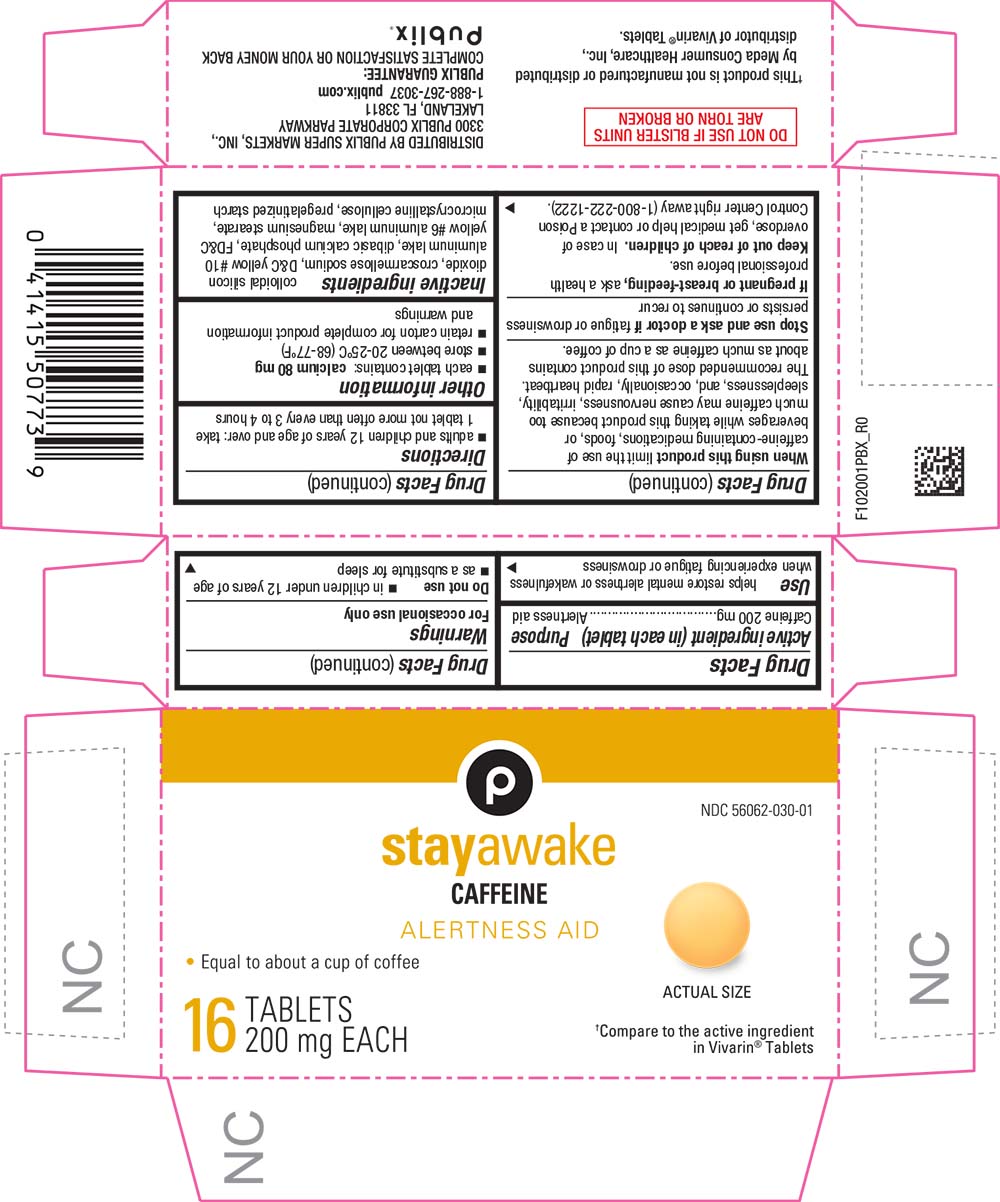 DRUG LABEL: stay awake
NDC: 56062-030 | Form: TABLET
Manufacturer: PUBLIX SUPER MARKETS INC
Category: otc | Type: HUMAN OTC DRUG LABEL
Date: 20241024

ACTIVE INGREDIENTS: CAFFEINE 200 mg/1 1
INACTIVE INGREDIENTS: SILICON DIOXIDE; CROSCARMELLOSE SODIUM; D&C YELLOW NO. 10; ALUMINUM OXIDE; CALCIUM PHOSPHATE, DIBASIC, ANHYDROUS; FD&C YELLOW NO. 6; MAGNESIUM STEARATE; CELLULOSE, MICROCRYSTALLINE; STARCH, PREGELATINIZED CORN

PBX-1020-2021-1104

Drug Facts

Active ingredient (in each tablet)

Caffeine 200 mg

Purpose

Alertness aid

Use

helps restore mental alertness or wakefulness when experiencing fatigue or drowsiness

Warnings

For occasional use only

Do not use

- in children under 12 years of age
- as a substitute for sleep

When using this product limit the use of caffeine-containing medications, foods, or beverages while taking this product because too much caffeine may cause nervousness, irritability, sleeplessness, and, occasionally, rapid heartbeat. The recommended dose of this product contains about as much caffeine as a cup of coffee.

Stop use and ask a doctor if fatigue or drowsiness persists or continues to recur

PREGNANCY OR BREAST FEEDING

If pregnant or breast-feeding, ask a health professional before use.

Keep out of reach of children. In case of overdose, get medical help or contact a Poison Control Center right away (1-800-222-1222).

Directions

- adults and children 12 years of age and over: take 1 tablet not more often than every 3 to 4 hours

Other information

- each tablet contains: calcium 80 mg
- store between 20-25°C (68-77°F)
- retain carton for complete product information and warnings

Inactive ingredients

colloidal silicon dioxide, croscarmellose sodium, D&C yellow #10 aluminum lake, dibasic calcium phosphate, FD&C yellow #6 aluminum lake, magnesium stearate, microcrystalline cellulose, pregelatinized starch

PRINCIPAL DISPLAY PANEL

NDC 56062-030-01

P

stayawake

CAFFEINE

ALERTNESS AID

• Equal to about a cup of coffee

Actual Size

16 TABLETS

200 mg EACH

†Compare to the active ingredient in Vivarin® Tablets